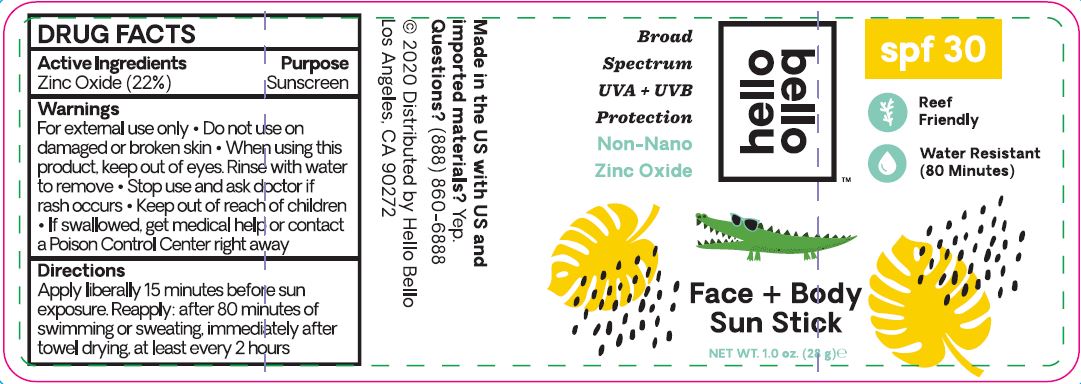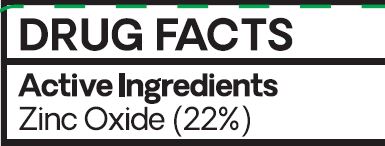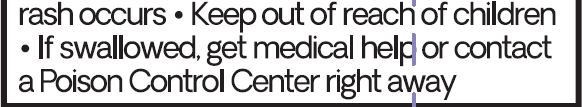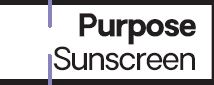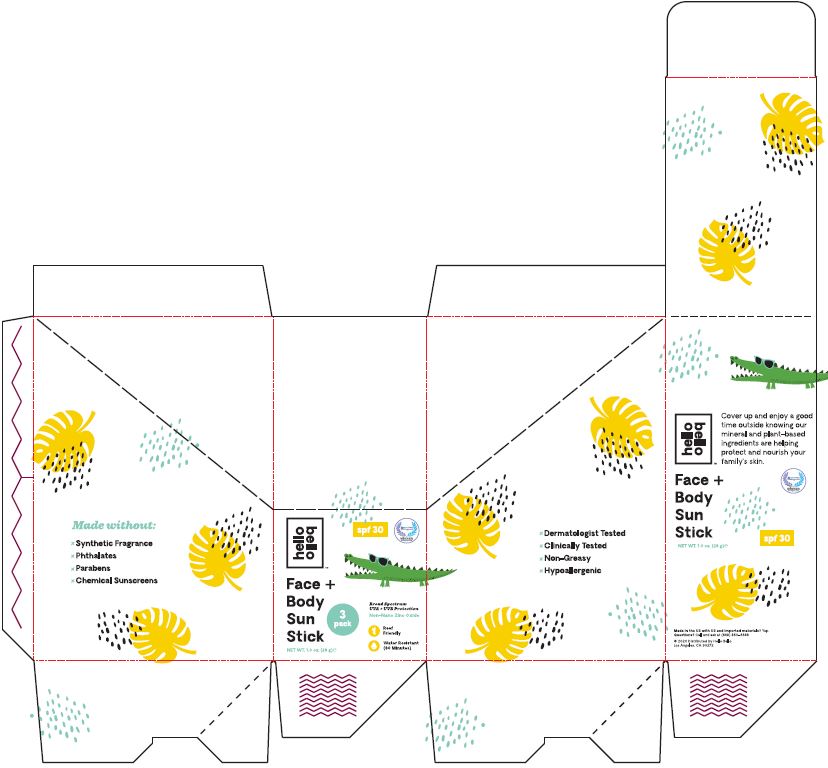 DRUG LABEL: Sunscreen
NDC: 62932-231 | Form: STICK
Manufacturer: Private Label Select Ltd CO
Category: otc | Type: HUMAN OTC DRUG LABEL
Date: 20220104

ACTIVE INGREDIENTS: ZINC OXIDE 22 g/100 g
INACTIVE INGREDIENTS: CANDELILLA WAX; COCOA BUTTER; .ALPHA.-TOCOPHEROL, D-; .DELTA.-TOCOPHEROL; COCONUT OIL; CARNAUBA WAX; SUNFLOWER OIL; ALOE VERA LEAF; SHEA BUTTER; .GAMMA.-TOCOPHEROL; CASTOR OIL; .BETA.-TOCOPHEROL; RASPBERRY SEED OIL

Hello Bello SPF 30 Mineral Sunscreen